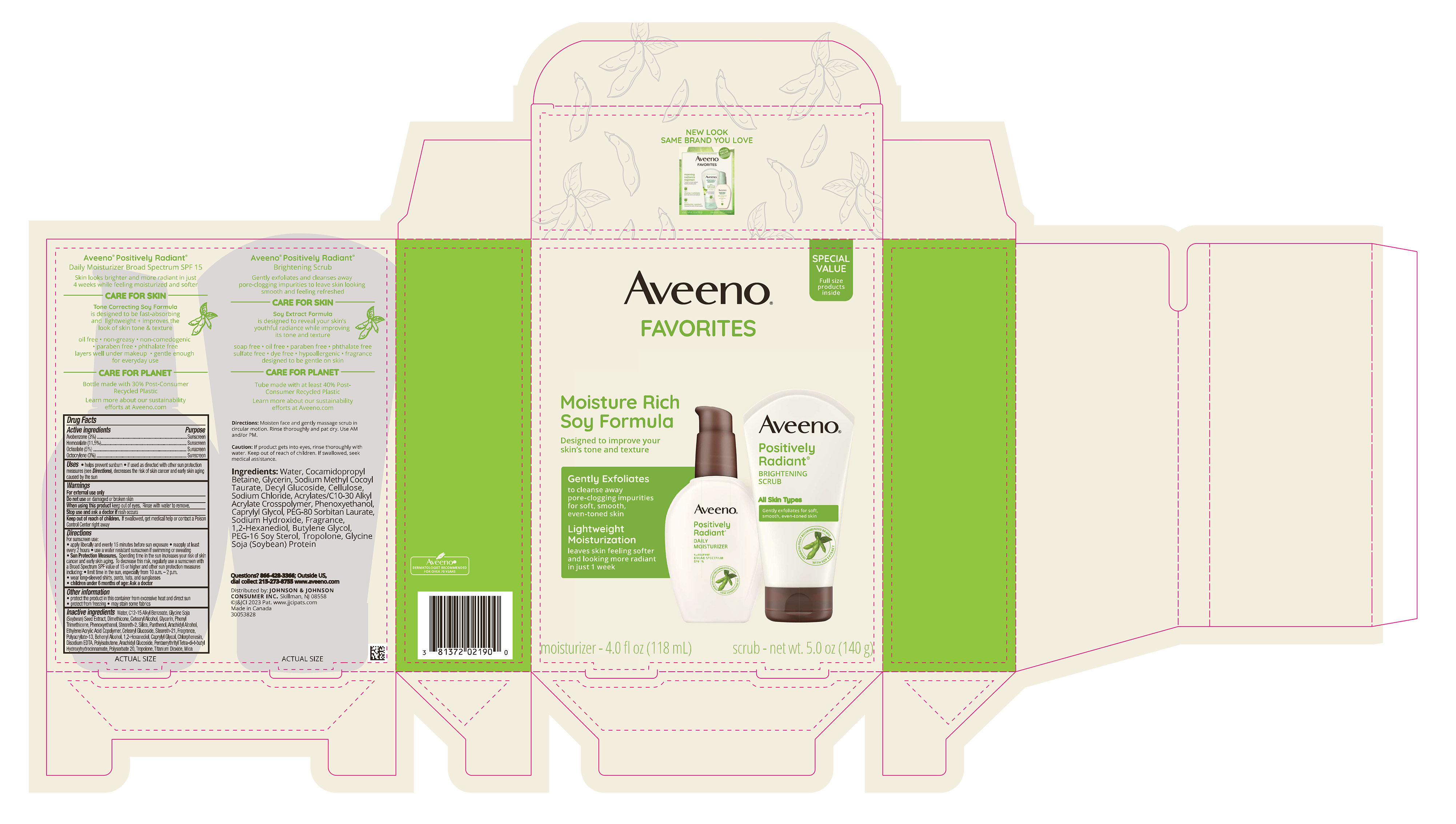 DRUG LABEL: Aveeno Favorites
NDC: 69968-0800 | Form: KIT | Route: TOPICAL
Manufacturer: Kenvue Brands LLC
Category: otc | Type: HUMAN OTC DRUG LABEL
Date: 20251106

ACTIVE INGREDIENTS: HOMOSALATE 115 mg/1 mL; OCTOCRYLENE 30 mg/1 mL; AVOBENZONE 30 mg/1 mL; OCTISALATE 50 mg/1 mL
INACTIVE INGREDIENTS: CETEARYL GLUCOSIDE; EDETATE DISODIUM ANHYDROUS; ARACHIDYL GLUCOSIDE; POLYSORBATE 20; DOCOSANOL; PHENYL TRIMETHICONE; WATER; ALKYL (C12-15) BENZOATE; SOYBEAN; DIMETHICONE; CETOSTEARYL ALCOHOL; PHENOXYETHANOL; STEARETH-2; PANTHENOL; 1,2-HEXANEDIOL; ARACHIDYL ALCOHOL; SILICON DIOXIDE; GLYCERIN; ACRYLIC ACID/ETHYLENE COPOLYMER (600 MPA.S); STEARETH-21; CAPRYLYL GLYCOL; CHLORPHENESIN; PENTAERYTHRITOL TETRAKIS(3-(3,5-DI-TERT-BUTYL-4-HYDROXYPHENYL)PROPIONATE); TROPOLONE; TITANIUM DIOXIDE; MICA

Aveeno Favorites KIT

Aveeno Positively Radiant Daily Moisturizer Sunscreen Broad Spectrum SPF 15

Drug Facts

Active ingredients

Avobenzone (3%)

Homosalate (11.5%)

Octisalate (5%)

Octocrylene (3%)

Purpose

Sunscreen

Uses

- helps prevent sunburn
- if used as directed with other sun protection measures (see Directions), decreases the risk of skin cancer an early skin aging caused by the sun

Warnings

For external use only

Do not use on damaged or broken skin

When using this product keep out of eyes. Rinse with water to remove.

Stop use and ask a doctor if rash occurs

Keep out of reach of children. If swallowed, get medical help or contact a Poison Control Center right away

Directions

For sunscreen use:

- apply liberally and evenly 15 minutes before sun exposure
- reapply at least every 2 hours
- use a water resistant sunscreen if swimming or sweating
- Sun Protection Measures. Spending time in the sun increases your risk of skin cancer and early skin aging. To decrease this risk, regularly use a sunscreen with a Broad Spectrum SPF value of 15 or higher and other sun protection measures including:
- limit time in the sun, especially from 10 a.m. - 2 p.m.
- wear long-sleeved shirts, pants, hats, and sunglasses
- children under 6 months of age: Ask a doctor

Other information

- protect the product in this container from excessive heat and direct sun
- protect from freezing
- may stain some fabrics

Inactive ingredients

Water, C12-15 Alkyl Benzoate, Glycine Soja (Soybean) Seed Extract, Dimethicone, Cetearyl Alcohol, Glycerin, Phenyl Trimethicone, Phenoxyethanol, Steareth-2, Silica, Panthenol, Arachidyl Alcohol, Ethylene/Acrylic Acid Copolymer, Cetearyl Glucoside, Steareth-21, Fragrance, Polyacrylate-13, Behenyl Alcohol, 1,2-Hexanediol, Caprylyl Glycol, Chlorphenesin, Disodium EDTA, Polyisobutene, Arachidyl Glucoside, Pentaerythrityl Tetra-di-t-butyl Hydroxyhydrocinnamate, Polysorbate 20, Tropolone, Titanium Dioxide, Mica

Questions?

866-428-3366; Outside US, dial collect 215-273-8755 www.aveeno.com

Distributed by:
JOHNSON & JOHNSON CONSUMER INC.
Skillman, NJ 08558

PRINCIPAL DISPLAY PANEL - Kit Package

Aveeno®

FAVORITES

SPECIAL

VALUE

Full size

products

inside

Moisture Rich

Soy Formula

Designed to improve your

skin’s tone and texture

Gently Exfoliates

to cleanse away

pore-clogging impurities

for soft, smooth,

even-toned skin

Lightweight

Moisturization

leaves skin feeling softer

and looking more radiant

in just 1 week

moisturizer - 4.0 fl oz (118 mL)

scrub - net wt. 5.0 oz (140 g)